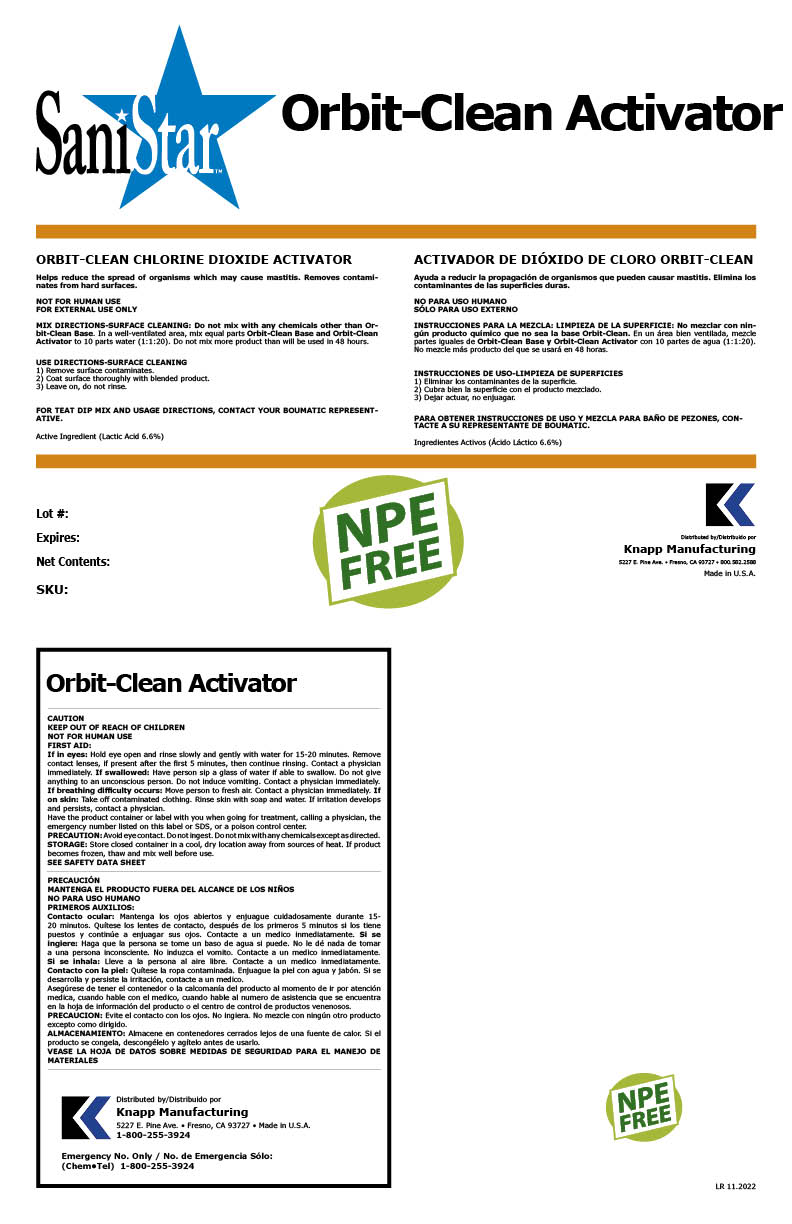 DRUG LABEL: Orbit Clean Activator
NDC: 43104-2016 | Form: LIQUID
Manufacturer: Knapp Manufacturing, Inc.
Category: animal | Type: OTC ANIMAL DRUG LABEL
Date: 20221122

ACTIVE INGREDIENTS: LACTIC ACID 0.066 kg/1 kg
INACTIVE INGREDIENTS: SODIUM XYLENESULFONATE; C8-10 ALCOHOLS; WATER

Orbit Clean Activator

Claim of effectiveness

Helps reduce the spread of organisms which may cause mastitis. Removes contaminates
from hard surfaces.

Use Directions

NOT FOR HUMAN USE
FOR EXTERNAL USE ONLY
MIX DIRECTIONS-SURFACE CLEANING: Do not mix with any chemicals other than Orbit-
Clean Base. In a well-ventilated area, mix equal parts Orbit-Clean Base and Orbit-Clean
Activator to 10 parts water (1:1:20). Do not mix more product than will be used in 48 hours.
USE DIRECTIONS-SURFACE CLEANING
1) Remove surface contaminates.
2) Coat surface thoroughly with blended product.
3) Leave on, do not rinse.
FOR TEAT DIP MIX AND USAGE DIRECTIONS, CONTACT YOUR BOUMATIC REPRESENTATIVE.

First Aid

If in eyes: Hold eye open and rinse slowly and gently with water for 15-20 minutes. Remove
contact lenses, if present after the first 5 minutes, then continue rinsing. Contact a physician
immediately. If swallowed: Have person sip a glass of water if able to swallow. Do not give
anything to an unconscious person. Do not induce vomiting. Contact a physician immediately.
If breathing difficulty occurs: Move person to fresh air. Contact a physician immediately. If
on skin: Take off contaminated clothing. Rinse skin with soap and water. If irritation develops
and persists, contact a physician.
Have the product container or label with you when going for treatment, calling a physician, the
emergency number listed on this label or SDS, or a poison control center.

Precautions & Hazards

KEEP OUT OF REACH OF CHILDREN
NOT FOR HUMAN USE

Avoid eye contact. Do not ingest. Do not mix with any chemicals except as directed.

General Storage

Store closed container in a cool, dry location away from sources of heat. If product
becomes frozen, thaw and mix well before use.

Claim of effectiveness.

Helps reduce the spread of organisms which may cause Mastitis.